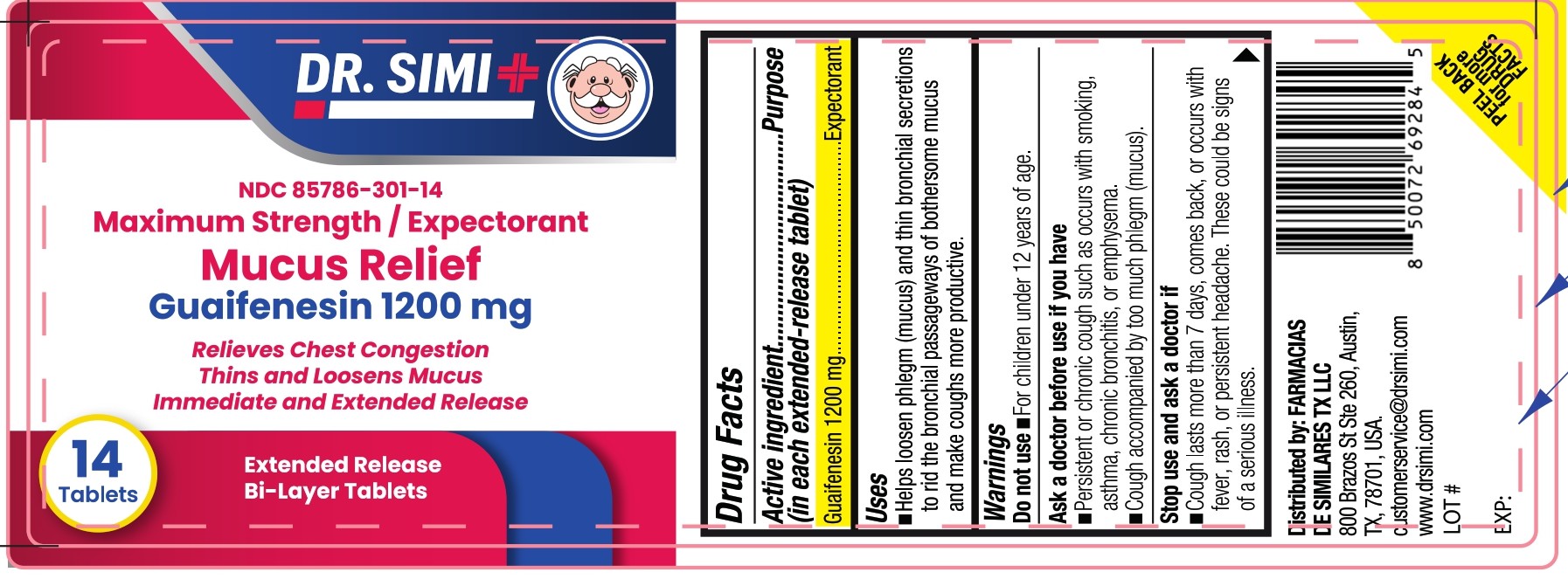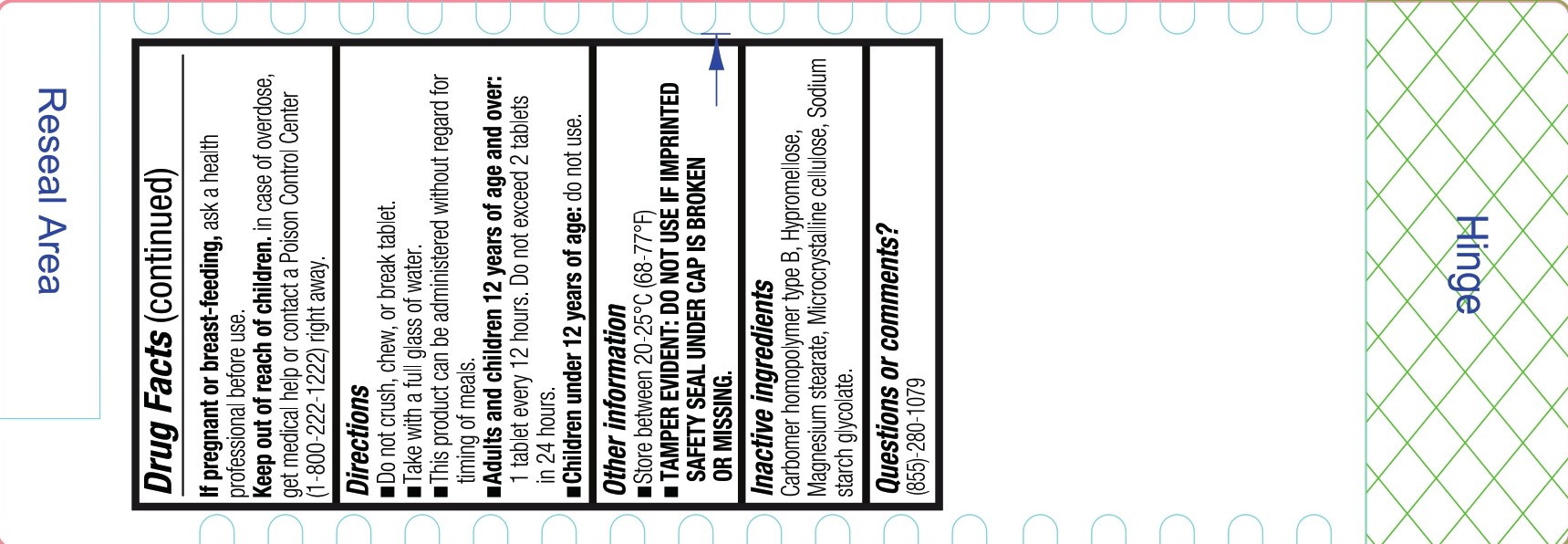 DRUG LABEL: Dr Simi Mucus Relief Expectorant
NDC: 85786-301 | Form: TABLET, EXTENDED RELEASE
Manufacturer: Farmacias De Similares TX LLC
Category: otc | Type: HUMAN OTC DRUG LABEL
Date: 20250815

ACTIVE INGREDIENTS: GUAIFENESIN 1200 mg/1 1
INACTIVE INGREDIENTS: SODIUM STARCH GLYCOLATE TYPE B; CARBOMER HOMOPOLYMER TYPE B (ALLYL PENTAERYTHRITOL OR ALLYL SUCROSE CROSSLINKED); MICROCRYSTALLINE CELLULOSE; HYPROMELLOSE, UNSPECIFIED; MAGNESIUM STEARATE

Maximum Strength Expectorant Mucus Relief Guaifenesin 1200

Drug Facts

Active ingredient (in each extended-release tablet)

- Guaifenesin 1200 mg

Purpose

- Expectorant

Uses

- Helps loosen phlegm (mucus) and thin bronchial secretions to rid the bronchial passageways of bothersome mucus and make coughs more productive.

Warnings

Do not use

- For children under 12 years of age.

Ask a doctor before use if you have

- Persistent or chronic cough such as occurs with smoking, asthma, chronic bronchitis, or emphysema.
- Cough accompained by too much phlegm (mucus).

Stop use and ask a doctor if

- Cough lasts more than 7 days, come back, or occurs with fever, rash or persistent headache. These could be signs of a serious illness.

If pregnant or breast-feeding

ask a health professional before use

Keep out of reach of children

Overdosage

in case of overdose, get medical help or contact a Poison Control Center (1-800-222-1222) right away.

Directions

- Do not crush, chew, or break tablet.
- Take with a full glass of water.
- This product can be administered without regard for timing of meals.

DOSAGE AND ADMINISTRATION

- Adults and children 12 years of age and over: 1 tablet every 12 hours. Do not exceed 2 tablets in 24 hours.
- Childrens under 12 years of age: do not use.

Other information

- Store between 20-25°C (68-77°F)
- TAMPER EVIDENT: DO NOT USE IF IMPRINTED SAFETY SEAL UNDER CAP IS BROKEN OR MISSING.

Inactive ingredients

Carbomer homopolymer type B, Hypromellose, Magnesium stearate, Microcrystalline cellulose, Sodium starch glycolate.

Questions or comments?

(855)-280-1079

Distributed by: FARMACIAS DE SIMILARES TX LLC
800 Brazos St Ste 260, Austin, TX, 78701, USA.
customerservice@drsimi.com
www.drsimi.com
LOT#

EXP:

PEEL BACK for more DRUG FACTS

PACKAGE LABEL

DR SIMI

NDC 85786-301-14

Maximum Strength / Expectorant

Mucus Relief

Guaifenesin 1200 mg

Relieves Chest Congestion

Thins and Loosens Mucus

Immediate and Extended Release

14 Tablets

Extended Release

Bi-Layer Tablets